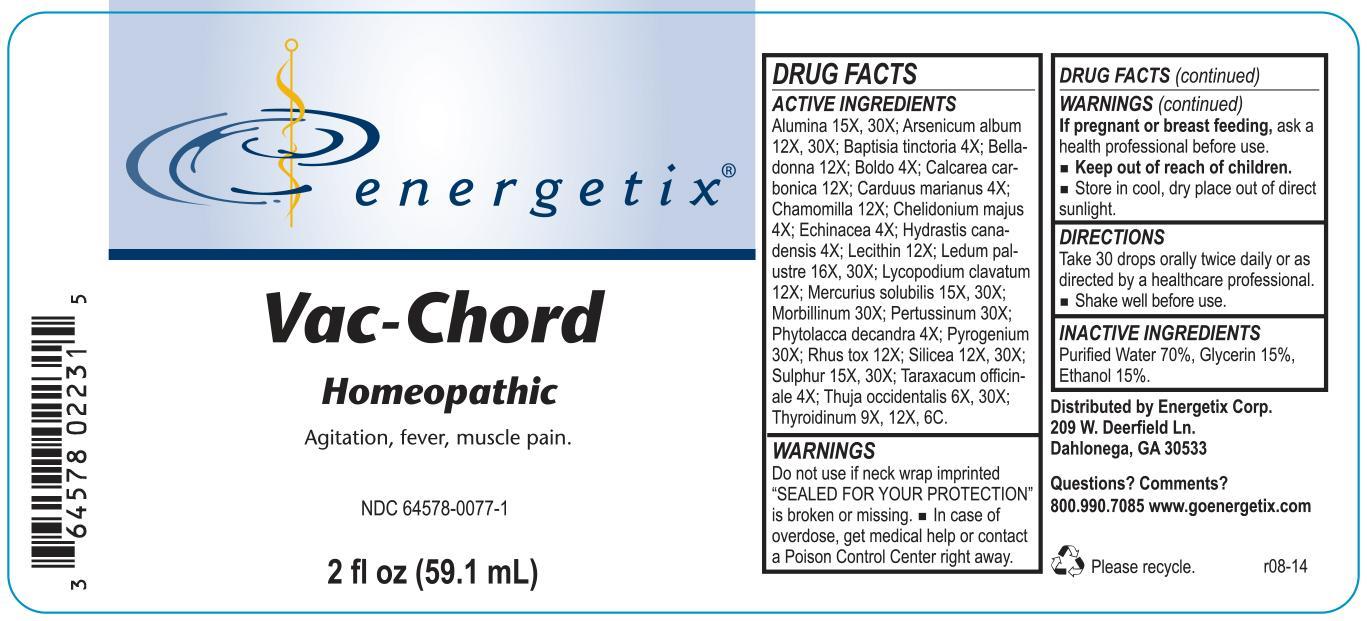 DRUG LABEL: Vac-Chord
NDC: 64578-0077 | Form: LIQUID
Manufacturer: Energetix Corp
Category: homeopathic | Type: HUMAN OTC DRUG LABEL
Date: 20140620

ACTIVE INGREDIENTS: ALUMINUM OXIDE 15 [hp_X]/59.1 mL; ARSENIC TRIOXIDE 12 [hp_X]/59.1 mL; BAPTISIA TINCTORIA ROOT 4 [hp_X]/59.1 mL; ATROPA BELLADONNA 12 [hp_X]/59.1 mL; PEUMUS BOLDUS LEAF 4 [hp_X]/59.1 mL; OYSTER SHELL CALCIUM CARBONATE, CRUDE 12 [hp_X]/59.1 mL; MILK THISTLE 4 [hp_X]/59.1 mL; MATRICARIA RECUTITA 12 [hp_X]/59.1 mL; CHELIDONIUM MAJUS 4 [hp_X]/59.1 mL; ECHINACEA ANGUSTIFOLIA 4 [hp_X]/59.1 mL; GOLDENSEAL 4 [hp_X]/59.1 mL; EGG PHOSPHOLIPIDS 12 [hp_X]/59.1 mL; LEDUM PALUSTRE TWIG 16 [hp_X]/59.1 mL; LYCOPODIUM CLAVATUM SPORE 12 [hp_X]/59.1 mL; MERCURIUS SOLUBILIS 15 [hp_X]/59.1 mL; MEASLES VIRUS 30 [hp_X]/59.1 mL; HUMAN SPUTUM, BORDETELLA PERTUSSIS INFECTED 30 [hp_X]/59.1 mL; PHYTOLACCA AMERICANA ROOT 4 [hp_X]/59.1 mL; RANCID BEEF 30 [hp_X]/59.1 mL; TOXICODENDRON PUBESCENS LEAF 12 [hp_X]/59.1 mL; SILICON DIOXIDE 12 [hp_X]/59.1 mL; SULFUR 15 [hp_X]/59.1 mL; TARAXACUM OFFICINALE 4 [hp_X]/59.1 mL; THUJA OCCIDENTALIS LEAFY TWIG 6 [hp_X]/59.1 mL; THYROID, UNSPECIFIED 9 [hp_X]/59.1 mL
INACTIVE INGREDIENTS: WATER 41.357 mL/59.1 mL; GLYCERIN 8.862 mL/59.1 mL; ALCOHOL 8.862 mL/59.1 mL

Vac-Chord

ACTIVE INGREDIENT

Alumina 15X, 30X; Arsenicum album 12X, 30X; Baptisia tinctoria 4X; Belladonna 12X; Boldo 4X; Calcarea carbonica 12X; Carduus marianus 4X; Chamomilla 12X; Chelidonium majus 4X; Echinacea 4X; Hydrastis canadensis 4X; Lecithin 12X; Ledum palustre 16X, 30X; Lycopodium clavatum 12X; Mercurius solubilis 15X, 30X; Morbillinum 30X; Pertussinum 30X; Phytolacca decandra 4X; Pyrogenium 30X; Rhus tox 12X; Silicea 12X, 30X; Sulphur 15X, 30X; Taraxacum officinale 4X; Thuja occidentalis 6X, 30X; Thyroidinum 9X, 12X, 6C.

Do not use if neck wrap imprinted "SEALED FOR YOUR PROTECTION" is broken or missing.

OVERDOSAGE

In case of overdose, get medical help or contact a Poison Control Center right away.

PREGNANCY OR BREAST FEEDING

If pregnant or breast feeding, ask a health professional before use.

Keep out of reach of children.

STORAGE AND HANDLING

Store in cool, dry place out of direct sunlight.

Questions? Comments?
800.990.7085 www.goenergetix.com

PURPOSE

Agitation, fever, muscle pain.

INACTIVE INGREDIENT

Purified Water 70%, Glycerin 15%, Ethanol 15%.

DOSAGE AND ADMINISTRATION

Take 30 drops orally twice daily or as directed by a healthcare professional. Shake well before use.

INDICATIONS AND USAGE

Agitation, fever, muscle pain.